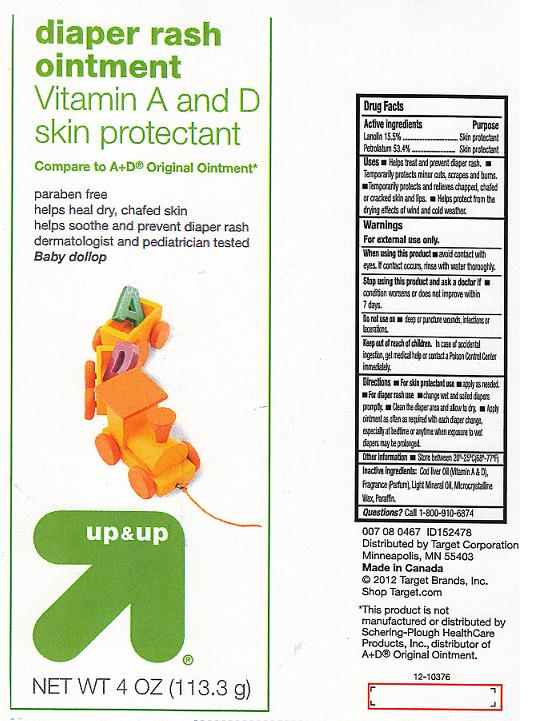 DRUG LABEL: UP AND UP
NDC: 11673-340 | Form: OINTMENT
Manufacturer: TARGET CORPORATION
Category: otc | Type: HUMAN OTC DRUG LABEL
Date: 20120501

ACTIVE INGREDIENTS: LANOLIN 15.5 g/100 g; PETROLATUM 53.4 g/100 g
INACTIVE INGREDIENTS: COD LIVER OIL; LIGHT MINERAL OIL; MICROCRYSTALLINE WAX; PARAFFIN

DRUG FACTS BOX

ACTIVE INGREDIENTS

LANOLIN 15.5%

PETROLATUM 53.4%

PURPOSE

SKIN PROTECTANT

SKIN PROTECTANT

USES

HELPS TREAT AND PREVENT DIAPER RASH. TEMPORARILY PROTECTS MINOR CUTS, SCRAPES AND BURNS. TEMPORARILY PROTECTS AND RELIEVES CHAPPED, CHAFED OR CRACKED SKIN AND LIPS. HELPS PROTECT FROM THE DRYING EFFECTS OF WIND AND COLD WEATHER.

WARNINGS

FOR EXTERNAL USE ONLY.

WHEN USING THIS PRODUCT

AVOID CONTACT WITH EYES. IF CONTACT OCCURS, RINSE WITH WATER THOROUGHLY.

STOP USING THIS PRODUCT AND ASK A DOCTOR IF

CONDITION WORSENS OR DOES NOT IMPROVE WITHIN 7 DAYS.

DO NOT USE ON

DEEP OR PUNCTURE WOUNDS, INFECTIONS OR LACERATIONS.

KEEP OUT OF REACH OF CHILDREN

IN CASE OF ACCIDENTAL INGESTION, GET MEDICAL HELP OR CONTACT A POISON CONTROL CENTER IMMEDIATELY.

DIRECTIONS

FOR SKIN PROTECTANT USE APPLY AS NEEDED. FOR DIAPER RASH USE, CHANGE WET AND SOILED DIAPERS PROMPTLY. CLEAN THE DIAPER AREA AND ALLOW TO DRY.APPLY OINTMENT AS OFTEN AS REQUIRED WITH EACH DIAPER CHANGE, ESPECIALLY AT BEDTIME OR ANYTIME WHEN EXPOSURE TO WET DIAPERS MAY BE PROLONGED.

OTHER INFORMATION

STORE BETWEEN 20-25C (58-77F).

INACTIVE INGREDIENTS:

COD LIVER OIL (VITAMIN A AND D), FRAGRANCE (PARFUM), LIGHT MINERAL OIL, MICROCRYSTALLINE WAX, PARAFFIN.

QUESTIONS?

CALL 1-800-910-6374.